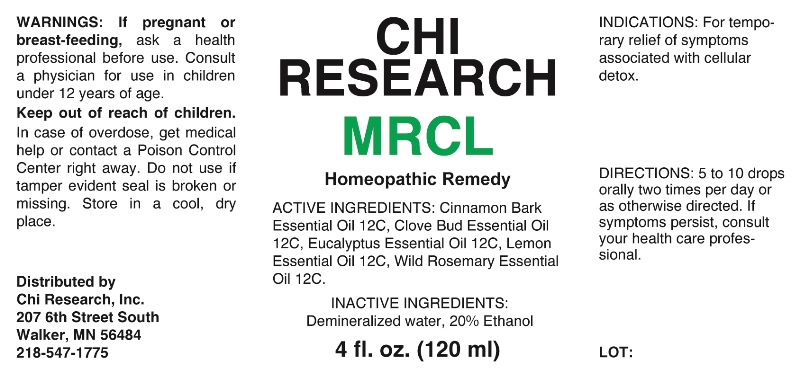 DRUG LABEL: MRCL
NDC: 52654-0005 | Form: LIQUID
Manufacturer: Chi Research, Inc.
Category: homeopathic | Type: HUMAN OTC DRUG LABEL
Date: 20240716

ACTIVE INGREDIENTS: CINNAMON BARK OIL 12 [hp_C]/1 mL; CLOVE OIL 12 [hp_C]/1 mL; EUCALYPTUS OIL 12 [hp_C]/1 mL; LEMON OIL 12 [hp_C]/1 mL; ROSEMARY OIL 12 [hp_C]/1 mL
INACTIVE INGREDIENTS: WATER; ALCOHOL

DRUG FACTS:

ACTIVE INGREDIENTS:

Cinnamon Bark Essential Oil 12C, Clove Bud Essential Oil 12C, Eucalyptus Essential Oil 12C, Lemon Essential Oil 12C, Wild Rosemary Essential Oil 12C.

INDICATIONS:

For temporary relief of symptoms associated with cellular detox.

WARNINGS:

If pregnant or breast-feeding, ask a health professional before use.

Consult a physician for use in children under 12 years of age.

Keep out of reach of children. In case of overdose, get medical help or contact a Poison Control Center right away.

Do not use if tamper evident seal is broken or missing.

Store in a cool, dry place.

KEEP OUT OF REACH OF CHILDREN:

In case of overdose, get medical help or contact a Poison Control Center right away.

DIRECTIONS:

5 to 10 drops orally two times per day or as otherwise directed. If symptoms persist, consult your health care professional.

INDICATIONS:

For temporary relief of symptoms associated with cellular detox.

INACTIVE INGREDIENTS:

Demineralized Water, 20% Ethanol

QUESTIONS:

Distributed by

Chi Research, Inc.

207 6th Street South

Walker, MN 56484

218-547-1775

PACKAGE LABEL DISPLAY:

CHI
RESEARCH

MRCL

Homeopathic Remedy

4 fl. oz. (120 ml)